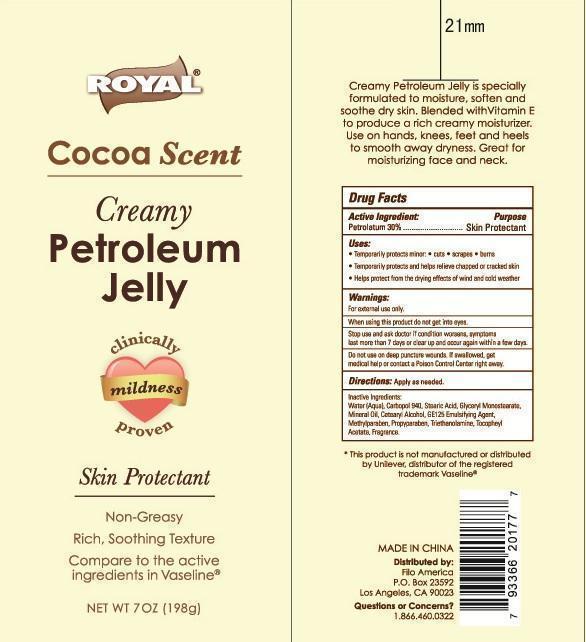 DRUG LABEL: Royal Petroleum (Cocoa Scent)
NDC: 50438-400 | Form: JELLY
Manufacturer: Filo America
Category: otc | Type: HUMAN OTC DRUG LABEL
Date: 20140219

ACTIVE INGREDIENTS: PETROLATUM 30 g/100 g
INACTIVE INGREDIENTS: WATER; STEARIC ACID; GLYCERYL MONOSTEARATE; MINERAL OIL; CETOSTEARYL ALCOHOL; METHYLPARABEN; PROPYLPARABEN; TROLAMINE; CARBOMER HOMOPOLYMER TYPE C

Drug Fact

Creamy petroleum Jelly is specially formulated to moisturize, soften and soothe dry skin. Blended with Vitamin E to produce a rich creamy moisturizer. Use on hands, knees, feet and heels to smooth away dryness. Great for moisturizing face and neck.

DRUG FACTS

Active Ingredient Purpose

Petrolatum 30% Skin Protectant

Purpose

Skin Protectant

INDICATIONS AND USAGE

Temporarily protects minor: cuts scrapes burns

Temporarily protects and helps relieve chapped or cracked skin

Helps protect from the drying effects of wind and cold weather

Warnings

For external use only. Do not use on deep puncture wounds.

When using this product, do not get into eyes

Stop use and ask doctor if condition worsens, Symptoms last more than 7 days clear up and occur again within a few days.

Keep out of reach of children. If swallowed, get medical help or contact a Poison Control Center right away.

DOSAGE AND ADMINISTRATION

Directions: apply as needed

Inactive ingredients:

water (Aqua), Carbopol 940, Stearic Acid, Glyceryl Monostearate, Mineral Oil, Cetearyl Alcohol, GE125 Emulsifying Agent, Methylparaben, Propyparaben, Triethanolamine, Tocopheryl Acetate, Cocoa Butter, Fragrance.

*This product is not manufactured or distributed by Unilever, distributor of the registered trademark Vaseline (r)

MADE IN CHINA

DISTRIBUTED BY:
Filo America

P.O. Box 23592

Los Angeles, CA 90023

Questions or Concerns?

1.866.460.0322